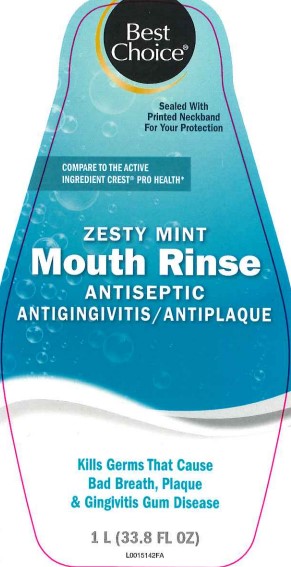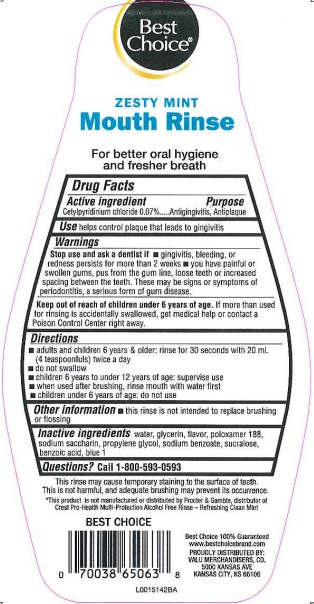 DRUG LABEL: ANTISEPTIC
NDC: 63941-299 | Form: RINSE
Manufacturer: Valu Merchandisers Company
Category: otc | Type: HUMAN OTC DRUG LABEL
Date: 20260216

ACTIVE INGREDIENTS: CETYLPYRIDINIUM CHLORIDE 0.7 mg/1 mL
INACTIVE INGREDIENTS: WATER; GLYCERIN; POLOXAMER 188; SACCHARIN SODIUM; PROPYLENE GLYCOL; SODIUM BENZOATE; SUCRALOSE; BENZOIC ACID; FD&C BLUE NO. 1

Best Choice 299.005/299AK-AL
Multi Action Alcohol Free Antiseptic Rinse w/CPC

Claims

Best Choice®

ZESTY MINT

Mouth Rinse

For better oral hygiene and fresher breath

Active ingredient

Cetylpyridinium chloride 0.07%

Purpose

Antigingivitis, Antiplaque

Use

helps control plaque that leads to gingivitis

Warnings

For this product

Stop use and ask a dentist if

- gingivitis, bleeding or redness persists for more than 2 weeks
- you have painful or swollen gums, pus from the gum line, loose teeth or increased spacing between the teeth. These may be signs or symptoms of periodontitis, a serious form of gum disease.

Keep out of reach of children under 6 years of age.

If more than used for rinsing is accidentally swallowed, get medical help or contact a Poison Control Center right away.

Directions

- adults and children 6 years & older: rinse for 30 seconds with 20 mL (4 teaspoonfuls) twice a day
- do not swallow
- children 6 years to under 12 years of age: supervise use
- when used after brushing, rinse mouth with water first
- children under 6 years of age: do not use

Other information

- this rinse is not intended to replace brushing or flossing

Inactive ingredients

water, glycerin, flavor, poloxamer 188, sodium saccharin, propylene glycol, sodium benzoate, sucralose, benzoic acid, blue 1

Questions?

Call 1-800-593-0593

Disclaimers

This rinse may cause temporary staining to the surface of teeth.

This is not harmful, and adequate brushing may prevent its occurrence.

*This product is not manufactured or distributed by Procter & Gamble, distributor of Crest Pro-Health Multi-Protection Alcohol Free Rinse - Refreshing Clean Mint

ADVERSE REACTIONS

Best Choice 100% Guaranteed

www.bestchoicebrand.com

PROUDLY DISTRIBUTED BY:

VALU MERCHANDISERS, CO.

5000 KANSAS AVE.

KANSAS CITY, KS 66106

principal display panel

Best Choice®

Sealed With Printed Neckband For Your Protection

COMPARE TO THE ACTIVE INGREDIENT CREST®PRO HEALTH*

ZESTY MINT

Mouth Rinse

ANTISEPTIC

ANTIGINGIVITIS/ANTIPLAQUE

Kills Germs That Cause Bad Breath, Plaque & Gingivitis Gum Disease

1 L (33.8 FL OZ)